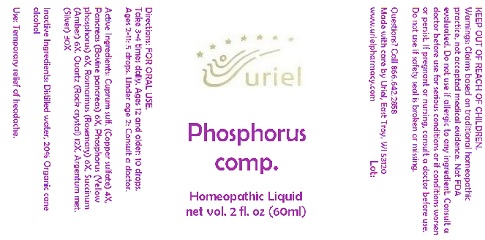 DRUG LABEL: Phosphorus comp.
NDC: 48951-8030 | Form: LIQUID
Manufacturer: Uriel Pharmacy Inc.
Category: homeopathic | Type: HUMAN OTC DRUG LABEL
Date: 20180430

ACTIVE INGREDIENTS: CUPRIC SULFATE 4 [hp_X]/1 mL; SUS SCROFA PANCREAS 6 [hp_X]/1 mL; PHOSPHORUS 6 [hp_X]/1 mL; ROSMARINUS OFFICINALIS FLOWERING TOP 6 [hp_X]/1 mL; AMBER 6 [hp_X]/1 mL; SILICON DIOXIDE 12 [hp_X]/1 mL; SILVER 30 [hp_X]/1 mL
INACTIVE INGREDIENTS: WATER; ALCOHOL

Phosphorus comp.

INDICATIONS AND USAGE

Directions: FOR ORAL USE ONLY.

DOSAGE AND ADMINISTRATION

Take 3-4 times daily. Ages 12 and older: 10 drops. Ages 2-11: 5 drops. Under age 2: Consult a doctor.

ACTIVE INGREDIENT

Active Ingredients: Cuprum sulf. (Copper sulfate) 4X, Pancreas (Bovine pancreas) 6X, Phosphorus (Yellow phosphorus) 6X, Rosmarinus (Rosemary) 6X, Succinum (Amber) 6X, Quartz (Rock crystal) 12X, Argentum met. (Silver) 30X

Inactive Ingredients: Distilled water, Organic cane alcohol

PURPOSE

Use: Temporary relief of headache.

KEEP OUT OF REACH OF CHILDREN.

WARNINGS

Warnings: Claims based on traditional homeopathic practice, not accepted medical evidence. Not FDA evaluated. Do not use if allergic to any ingredient. Consult a doctor before use for serious conditions or if conditions worsen or persist. If pregnant or nursing, consult a doctor before use. Do not use if safety seal is broken or missing.

QUESTIONS

Questions? Call 866.642.2858 Made with care by Uriel, East Troy, WI 53120 www.urielpharmacy.com